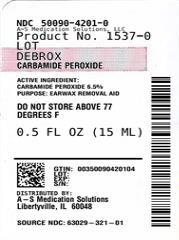 DRUG LABEL: DEBROX
NDC: 50090-4201 | Form: LIQUID
Manufacturer: A-S Medication Solutions
Category: otc | Type: HUMAN OTC DRUG LABEL
Date: 20250903

ACTIVE INGREDIENTS: CARBAMIDE PEROXIDE 65 mg/1 mL
INACTIVE INGREDIENTS: CITRIC ACID; GLYCERIN; PROPYLENE GLYCOL; SODIUM LAUROYL SARCOSINATE; AQUA

DEBROX 63029-321-01

Debrox Earwax Removal Aid

Drug Facts

Active ingredient

Carbamide peroxide 6.5% non USP

Purpose

Earwax removal aid

Uses

For occasional use as an aid to soften, loosen, and remove excessive earwax

Warnings

Ask a doctor before use if you have

ear drainage or discharge • ear pain

irritation or rash in the ear • dizziness

an injury or perforation (hole) of the eardrum • recently had ear surgery

When using this product

avoid contact with the eyes

Stop use and ask a doctor if

you need to use for more than four days

excessive earwax remains after use of this product

Keep this and all drugs out of the reach of children.

If swallowed, get medical help or contact a Poison Control Center (1-800-222-1222) right away.

Directions

FOR USE IN THE EAR ONLY

adults and children over 12 years of age:

tilt head sideways place 5 to 10 drops into ear tip of applicator should not enter ear canal keep drops in ear for several minutes by keeping head tilted or placing cotton in ear • use twice daily for up to four days if needed, or as directed by a doctor any wax remaining after treatment may be removed by gently flushing the ear with warm water, using a soft rubber bulb ear syringe

children under 12 years: consult a doctor

Other information

- do not store above 25C (77F)
- store bottle in the outer carton, in an upright position
- product foams on contact with earwax due to release of oxygen. There may be an associated “crackling” sound.
- keep tip on bottle when not in use

Inactive Ingredients

citric acid, flavor, glycerin, propylene glycol, sodium lauroyl sarcosinate, water

Questions?

1-866-255-5202 Debrox.com

HOW SUPPLIED

Product: 50090-4201

NDC: 50090-4201-0 15 mL in a BOTTLE, DROPPER / 1 in a CARTON